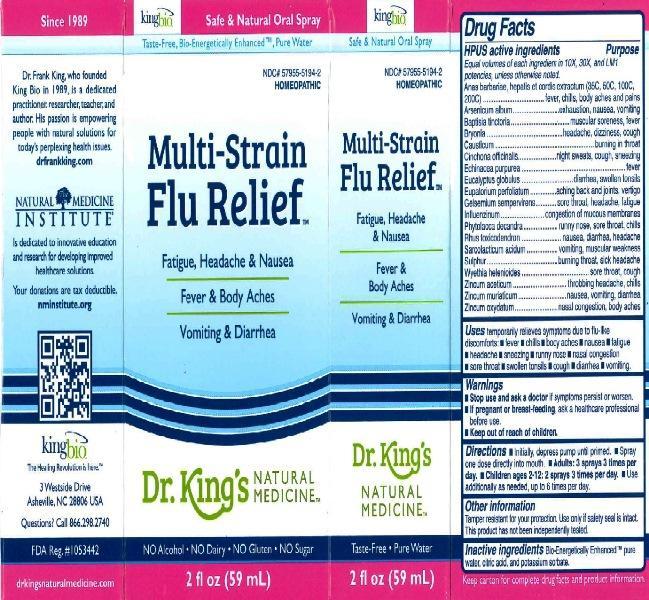 DRUG LABEL: Multi Strain Flu Relief
                
NDC: 57955-5194 | Form: LIQUID
Manufacturer: King Bio Inc.
Category: homeopathic | Type: HUMAN OTC DRUG LABEL
Date: 20161209

ACTIVE INGREDIENTS: CAIRINA MOSCHATA HEART/LIVER AUTOLYSATE 35 [hp_C]/59 mL; ARSENIC TRIOXIDE 10 [hp_X]/59 mL; BAPTISIA TINCTORIA ROOT 10 [hp_X]/59 mL; BRYONIA ALBA ROOT 10 [hp_X]/59 mL; EUCALYPTUS GLOBULUS LEAF 10 [hp_X]/59 mL; EUPATORIUM PERFOLIATUM FLOWERING TOP 10 [hp_X]/59 mL; GELSEMIUM SEMPERVIRENS ROOT 10 [hp_X]/59 mL; INFLUENZA A VIRUS 10 [hp_X]/59 mL; INFLUENZA B VIRUS 10 [hp_X]/59 mL; PHYTOLACCA AMERICANA ROOT 10 [hp_X]/59 mL; TOXICODENDRON PUBESCENS LEAF 10 [hp_X]/59 mL; LACTIC ACID, L- 10 [hp_X]/59 mL; SULFUR 10 [hp_X]/59 mL; WYETHIA HELENIOIDES ROOT 10 [hp_X]/59 mL; ZINC ACETATE ANHYDROUS 10 [hp_X]/59 mL; ZINC CHLORIDE 10 [hp_X]/59 mL; ZINC OXIDE 10 [hp_X]/59 mL
INACTIVE INGREDIENTS: WATER; ANHYDROUS CITRIC ACID; POTASSIUM SORBATE

Multi-Strain Flu Relief

HPUS Active Ingredients:

Equal volumes of each ingredient in 10X, 30X, and LM1 potencies unless otherwise specified. Anas barbariae, hepatis et cordis extractum (35C, 50C, 100C, 200C).

Anas barbariae, hepatis et cordis extractum, Arsenicum album, Baptisia tinctoria, Bryonia alba, Causticum, Cinchona officinalis, Echinacea purpurea, Eucalyptus globulus, Eupatorium perfoliatum, Gelsemium sempervirens, Influenzinum, Phytolacca decandra, Rhus toxicodendron, Sarcolacticum acidum, Sulphur, Wyethia helenioides, Zincum aceticum, Zincum muriaticum and Zincum oxydatum.

Inactive Ingredient:

Bio-Energetically Enhanced taste-free, pure water, citric acid, and potassium sorbate.

Directions:

- Initially, depress pump until primed.
- Spray one dose directly into mouth.
- Adult dose: 3 pump sprays 3 times per day.
- Children: 2-12 years 2 pump sprays 3 times per day.
- Use additionally as needed, as needed, up to 6 times per day.

Warnings:

- Stop use and ask a doctor if symptoms persist or worsen.
- If pregnant or breast-feeding, ask a healthcare professional before use.

- Keep out of reach of children.

Other Information:

Tamper resistant for your protection. Use only if safety seal is intact. This product has not been independently tested.

HPUS Active Ingredients Purpose

Anas barbariae, hepatis et cordis extractum......fever, chills, body aches and pains

Arsenicum album..............................................exhaustion, nausea, vomiting

Baptisia tinctoria...............................................muscular soreness, fever

Bryonia alba.....................................................headache, dizziness, cough

Causticum.......................................................burning in throat

Cinchona officinalis...........................................night sweats, cough, sneezing

Echinacea purpurea..........................................fever

Eucalyptus globulus..........................................diarrhea, swollen tonsils

Eupatorium perfoliatum.....................................aching back and joints, vertigo

Gelsemium sempervirens..................................sore throat, headache, fatigue

Influenzinum...................................................congestion of mucus membranes

Phytolacca decandra........................................runny nose, sore throat, chills

Rhus toxicodendron..........................................nausea, diarrhea, headache

Sarcolacticum acidum.......................................vomiting, muscular weakness

Sulphur............................................................burning throat, sick headache

Wyethia helenioides..........................................sore throat, cough

Zincum aceticum..............................................throbbing headache, chills

Zincum muriaticum...........................................nausea, vomiting, diarrhea

Zincum oxydatum.............................................nasal congestion, body aches

INDICATIONS AND USAGE

Uses temporarily relieves flu-like discomforts:

- fever
- chills
- night sweats
- nausea
- vomiting
- headache
- sneezing
- runny nose
- nasal congestion
- sore throat
- swollen tonsils
- cough
- diarrhea
- body aches
- fatigue

as per various homeopathic Materia Medicas